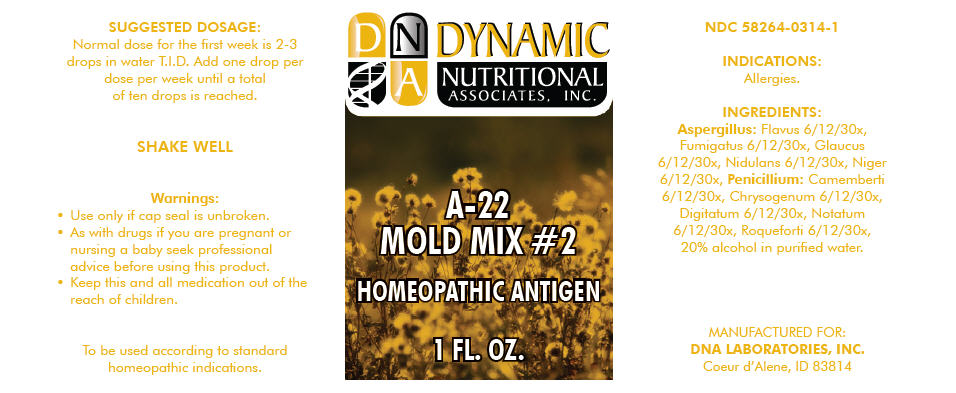 DRUG LABEL: A-22
NDC: 58264-0314 | Form: SOLUTION
Manufacturer: DNA Labs, Inc.
Category: homeopathic | Type: HUMAN OTC DRUG LABEL
Date: 20250109

ACTIVE INGREDIENTS: ASPERGILLUS FLAVUS 30 [hp_X]/1 mL; ASPERGILLUS FUMIGATUS 30 [hp_X]/1 mL; EUROTIUM HERBARIORUM 30 [hp_X]/1 mL; ASPERGILLUS NIDULANS 30 [hp_X]/1 mL; ASPERGILLUS NIGER VAR. NIGER 30 [hp_X]/1 mL; PENICILLIUM CAMEMBERTI 30 [hp_X]/1 mL; PENICILLIUM CHRYSOGENUM VAR. CHRYSOGENUM 30 [hp_X]/1 mL; PENICILLIUM DIGITATUM 30 [hp_X]/1 mL; PENICILLIUM ROQUEFORTI 30 [hp_X]/1 mL
INACTIVE INGREDIENTS: ALCOHOL; WATER

A-22

NDC 58264-0314-1

INDICATIONS

PURPOSE

Allergies.

INGREDIENTS

INACTIVE INGREDIENT

Aspergillus: Flavus 6/12/30x, Fumigatus 6/12/30x, Glaucus 6/12/30x, Nidulans 6/12/30x, Niger 6/12/30x, Penicillium: Camemberti 6/12/30x, Chrysogenum 6/12/30x, Digitatum 6/12/30x, Notatum 6/12/30x, Roqueforti 6/12/30x, 20% alcohol in purified water.

SUGGESTED DOSAGE

Normal dose for the first week is 2-3 drops in water T.I.D. Add one drop per dose per week until a total of ten drops is reached.

STORAGE AND HANDLING

SHAKE WELL

Warnings

- Use only if cap seal is unbroken.

PREGNANCY OR BREAST FEEDING

- As with drugs if you are pregnant or nursing a baby seek professional advice before using this product.

KEEP OUT OF REACH OF CHILDREN

- Keep this and all medication out of the reach of children.

To be used according to standard homeopathic indications.

PRINCIPAL DISPLAY PANEL - 1 FL. OZ. Bottle Label

DYNAMIC
NUTRITIONAL
ASSOCIATES, INC.

A-22
MOLD MIX #2

HOMEOPATHIC ANTIGEN

1 FL. OZ.